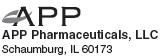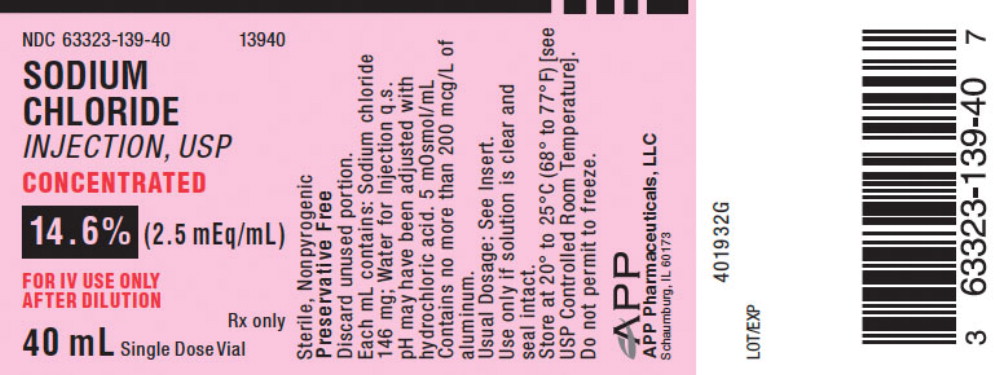 DRUG LABEL: Sodium Chloride
NDC: 63323-139 | Form: INJECTION, SOLUTION
Manufacturer: Fresenius Kabi USA, LLC
Category: prescription | Type: HUMAN PRESCRIPTION DRUG LABEL
Date: 20251128

ACTIVE INGREDIENTS: SODIUM CHLORIDE 146 mg/1 mL
INACTIVE INGREDIENTS: HYDROCHLORIC ACID

Sodium Chloride Injection USP

14.6% (2.5 mEq/mL)

CONCENTRATED SOLUTIONS FOR USE ONLY AFTER DILUTION WITH COMPATIBLE IV FLUIDS TO CORRECT SODIUM DEFICIENCY WHEN ORAL REPLACEMENT IS NOT FEASIBLE.

DESCRIPTION

Sodium Chloride Injection, USP is a sterile, nonpyrogenic, concentrated solution for intravenous administration ONLY AFTER DILUTION to replenish electrolytes. The preparation contains 2.5 mEq/mL (14.6%) sodium chloride, in Water for Injection. The solution contains no bacteriostat, antimicrobial agent or added buffer; pH of the solution ranges from 4.5 to 7.0. Each mL contains: Sodium chloride 146 mg; Water for Injection q.s. pH may have been adjusted with hydrochloric acid. The osmolar concentration of the 2.5 mEq/mL solution is 5 mOsmol/mL. Sodium chloride is chemically designated NaCI, a white crystalline compound freely soluble in water.

CLINICAL PHARMACOLOGY

Sodium chloride in water dissociates to provide sodium (Na ^+) and chloride (CI ^-) ions. These ions are normal constituents of the body fluids (principally extracellular) and are essential for maintaining electrolyte balance.

Sodium is the principal cation of extracellular fluid. It comprises more than 90% of the total cations at its normal plasma concentration of approximately 142 mEq/L. While the sodium ion can diffuse across cell membranes, intracellular sodium is maintained at a much lower concentration than extracellular sodium through the expenditure of energy by the cell (so-called ‘‘sodium cation pump’’). Loss of intracellular potassium ion is usually accompanied by an increase in intracellular sodium ion.

When serum sodium concentration is low, the secretion of antidiuretic hormone (ADH) by the pituitary is inhibited, thereby preventing water reabsorption by the distal renal tubules. On the other hand, adrenal secretion of aldosterone increases renal tubular reabsorption of sodium in an effort to reestablish normal serum sodium concentration.

Chloride (CI ^-) has an integral role in buffering action when oxygen and carbon dioxide exchange occurs in the red blood cells.

The distribution and excretion of sodium (Na ^+) and chloride (CI ^-) are largely under the control of the kidney which maintains a balance between intake and output.

INDICATIONS AND USAGE

Sodium Chloride Injection, USP is indicated for parenteral restoration of sodium ion in patients with restricted oral intake. Sodium replacement is specifically indicated in patients with hyponatremia or low salt syndrome. Sodium chloride injection may also be added to compatible carbohydrate solutions such as dextrose in water to provide electrolytes.

CONTRAINDICATIONS

Sodium chloride injection is contraindicated in patients with hypernatremia or fluid retention.

WARNINGS

WARNING: This product contains aluminum that may be toxic. Aluminum may reach toxic levels with prolonged parenteral administration if kidney function is impaired. Premature neonates are particularly at risk because their kidneys are immature, and they require large amounts of calcium and phosphate solutions, which contain aluminum.

Research indicates that patients with impaired kidney function, including premature neonates, who receive parenteral levels of aluminum at greater than 4 to 5 mcg/kg/day accumulate aluminum at levels associated with central nervous system and bone toxicity. Tissue loading may occur at even lower rates of administration.

Solutions containing sodium ions should be used with great care, if at all, in patients with congestive heart failure, severe renal insufficiency and in clinical states in which there exists edema with sodium retention.

In patients with diminished renal function, administration of solutions containing sodium may result in sodium retention.

The intravenous administration of this solution (after appropriate dilution) can cause fluid and/or solute overloading resulting in dilution of other serum electrolyte concentrations, overhydration, congested states or pulmonary edema.

Excessive administration of potassium free solutions may result in significant hypokalemia.

PRECAUTIONS

Do not use unless the solution is clear and seal is intact. Discard unused portion.

Sodium chloride injection must be diluted before infusion to avoid a sudden increase in the level of plasma sodium. Too rapid administration should be avoided.

Special caution should be used in administering sodium containing solutions to patients with severe renal impairment, cirrhosis of the liver, cardiac failure, or other edematous or sodium-retaining states.

Clinical evaluation and periodic laboratory determinations are necessary to monitor changes in fluid balance, electrolyte concentrations, and acid-base balance during prolonged parenteral therapy or whenever the condition of the patient warrants such evaluation.

Caution must be exercised in the administration of parenteral fluids, especially those containing sodium ions, to patients receiving corticosteroids or corticotropin.

Pregnancy

Teratogenic Effects: Pregnancy Category C—

Animal reproduction studies have not been conducted with sodium chloride. It is also not known whether sodium chloride can cause fetal harm when administered to a pregnant woman or can affect reproduction capacity. Sodium chloride should be given to a pregnant woman only if clearly needed.

ADVERSE REACTIONS

None known.

OVERDOSAGE

In the event of over hydration or solute overload, reevaluate the patient and institute appropriate corrective measures. (See WARNINGS and PRECAUTIONS.)

DOSAGE AND ADMINISTRATION

Sodium chloride injection is administered intravenously only after addition to a larger volume of fluid.

The dose, dilution and rate of injection are dependent upon the individual needs of each patient.

All or part of the contents of one or more additive containers may be added to an intravenous solution container. Concentrations of up to 5% sodium chloride have been administered.

Parenteral drug products should be inspected visually for particulate matter and discoloration prior to administration, whenever solution and container permit. (See PRECAUTIONS.)

HOW SUPPLIED

Sodium Chloride Injection, USP is available in flip-top glass vials.

Product; No. | NDC; No. | %; NaCl | Na ^+; mEq/mL | Cl ^-; mEq/mL | mOsmol/; mL | Fill Volume mL
13920 | 63323-139-20 | 14.6 | 2.5 | 2.5 | 5 | 20
13940 | 63323-139-40 | 14.6 | 2.5 | 2.5 | 5 | 40

These vials are Single Dose Vials; packaged 25 vials per tray.

Store at 20° to 25°C (68° to 77°F) [see USP Controlled Room Temperature]. Do not permit to freeze.

45873E

Revised: June 2008

PACKAGE LABEL

PACKAGE LABEL - PRINCIPAL DISPLAY - Sodium Chloride 40 mL Vial Label

NDC 63323-139-40

13940

Sodium Chloride Injection, USP

Concentrated

14.6% (2.5 mEq/mL)

For IV Use Only After Dilution

Rx only

40 mL Single Dose Vial